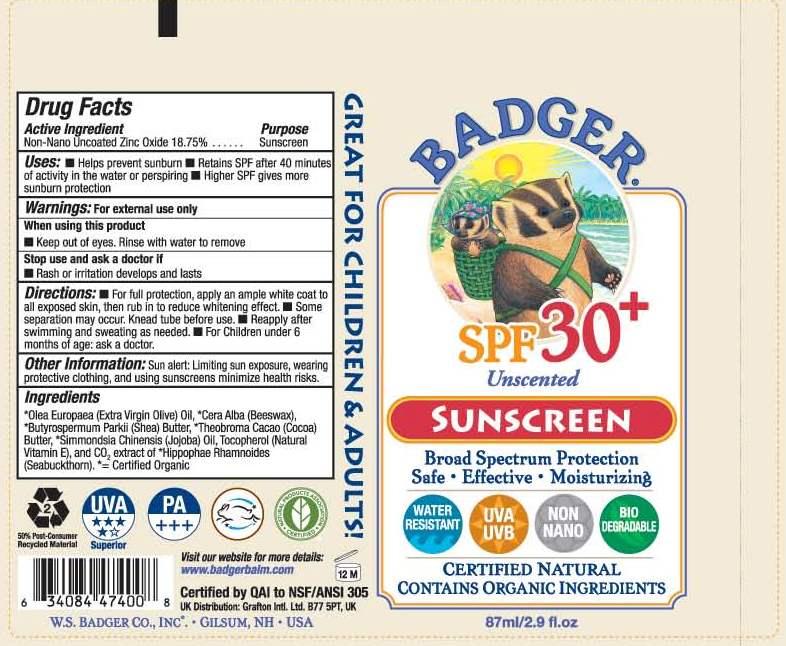 DRUG LABEL: Badger SPF30 Unscented Sunscreen
NDC: 51514-201 | Form: OINTMENT
Manufacturer: Autumn Harp, Inc.
Category: otc | Type: HUMAN OTC DRUG LABEL
Date: 20111110

ACTIVE INGREDIENTS: Zinc Oxide 18.75 mL/100 mL
INACTIVE INGREDIENTS: OLIVE OIL; YELLOW WAX; SHEA BUTTER; COCOA BUTTER; JOJOBA OIL; TOCOPHEROL; HIPPOPHAE RHAMNOIDES SEED OIL

Drug Facts

Active Ungredient

Non-Nano Uncoated Zinc Oxide 18.75%

Purpose

Sunscreen

Uses:

- Helps prevent sunburn
- Reatins SPF after 40 minutes of activity in the water or perspiring
- Higher SPF gives more sunburn protection

Warnings:

For external use only

When using this product

Keep out of eyes. Rinse with water to remove

Stop use and ask a doctor if

Rash pr irritation develops and lasts

Directions:

- For full protection, apply ample white coat to all exposed skin, then rub to reduce the whitening effect.
- Some separation may occur. Knead tube before use.
- Reapply after swimming and sweating as needed.
- For children under 6 months of age: ask a doctor